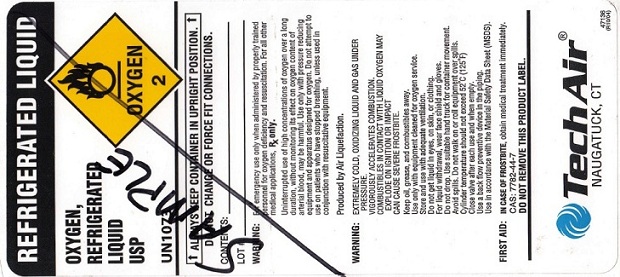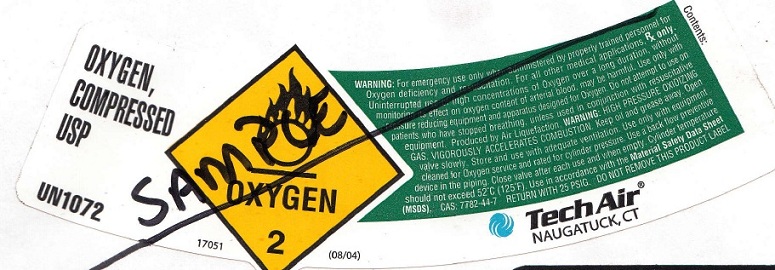 DRUG LABEL: Oxygen
                
NDC: 68624-001 | Form: GAS
Manufacturer: Tech Air of Naugatuck LLC
Category: prescription | Type: HUMAN PRESCRIPTION DRUG LABEL
Date: 20120827

ACTIVE INGREDIENTS: Oxygen 990 mL/1 L

Oxygen

PACKAGE LABEL

REFRIGERATED LIQUID
OXYGEN,
REFRIGERATED
LIQUID
USP
UN1073
OXYGEN 2
ALWAYS KEEP CONTAINER IN UPRIGHT POSITION.
DO NOT CHANGE OR FORCE FIT CONNECTIONS.
CONTENTS:
LOT #:
WARNING: For emergency use only when administered by properly trained personnel for oxygen deficiency and resuscitation. For all other medical applications, RX ONLY.
Uninterrupted use of high concentrations of oxygen over a long duration, without monitoring its effect on oxygen content of arterial blood, may be harmful. Use only with pressure reducing equipment and apparatus designed for oxygen. Do not attempt to use on patients who have stopped breathing, unless used in conjunction with resuscitative equipment.
Produced by Air Liquefaction.
WARNING: EXTREMELY COLD, OXIDIZING LIQUID AND GAS UNDER PRESSURE.
VIGOROUSLY ACCELERATES COMBUSTION.
COMBUSTIBLES IN CONTACT WITH LIQUID OXYGEN MAY EXPLODE ON IGNITION OR IMPACT
CAN CAUSE SEVERE FROSTBITE.
Keep oil, grease, and combustibles away.
Use only with equipment cleaned for oxygen service.
Store and use with adequate ventilation.
Do not get liquid in eyes, on skin, or clothing.
For liquid withdrawal, wear face shield and gloves.
Do not drop. Use suitable hand truck for container movement.
Avoid spills. Do not walk on or roll equipment over spills.
Cylinder temperature should not exceed 52 degrees C (125 degrees F)
Close valve after each use and when empty.
Use a back flow preventive device in the piping.
Use in accordance with the Material Safety Data Sheet (MSDS).
FIRST AID: IN CASE FROSTBITE, obtain medical treatment immediately.
CAS: 7782-44-7
DO NOT REMOVE THIS PRODUCT LABEL.
TechAir
NAUGATUCK, CT 47136 (R10/04)

PACKAGE LABEL

OXYGEN,
COMPRESSED
USP
UN1072
OXYGEN 2
17051 (08/04)
WARNING: For emergency use only when administered by properly trained personnel for oxygen deficiency and resuscitation. For all other medical applications, RX ONLY.
Uninterrupted use of high concentrations of oxygen over a long duration, without monitoring its effect on oxygen content of arterial blood, may be harmful. Use only with pressure reducing equipment and apparatus designed for oxygen. Do not attempt to use on patients who have stopped breathing, unless used in conjunction with resuscitative equipment.
Produced by Air Liquefaction.
WARNING: HIGH PREASSURE OXIDIZING GAS. VIGOROUSLY ACCELERATES COMBUSTION. Keep oil and grease away. Open valve slowly. Store and use with adequate ventilation. Use only with equipment cleared for oxygen services and rated for cylinder pressure. Use back flow preventive device in the piping. Close valve after each use and when empty. Cylender temperature should not exceed 52 degrees C (125 degrees F). Use in accordance with the Material Safety Data Sheet (MSDS).
CAS: 7782-44-7 RETURN WITH 25 PSIG. DO NOT REMOVE THIS PRODUCT LABEL.
TechAir
NAUGATUCK, CT
Contents: